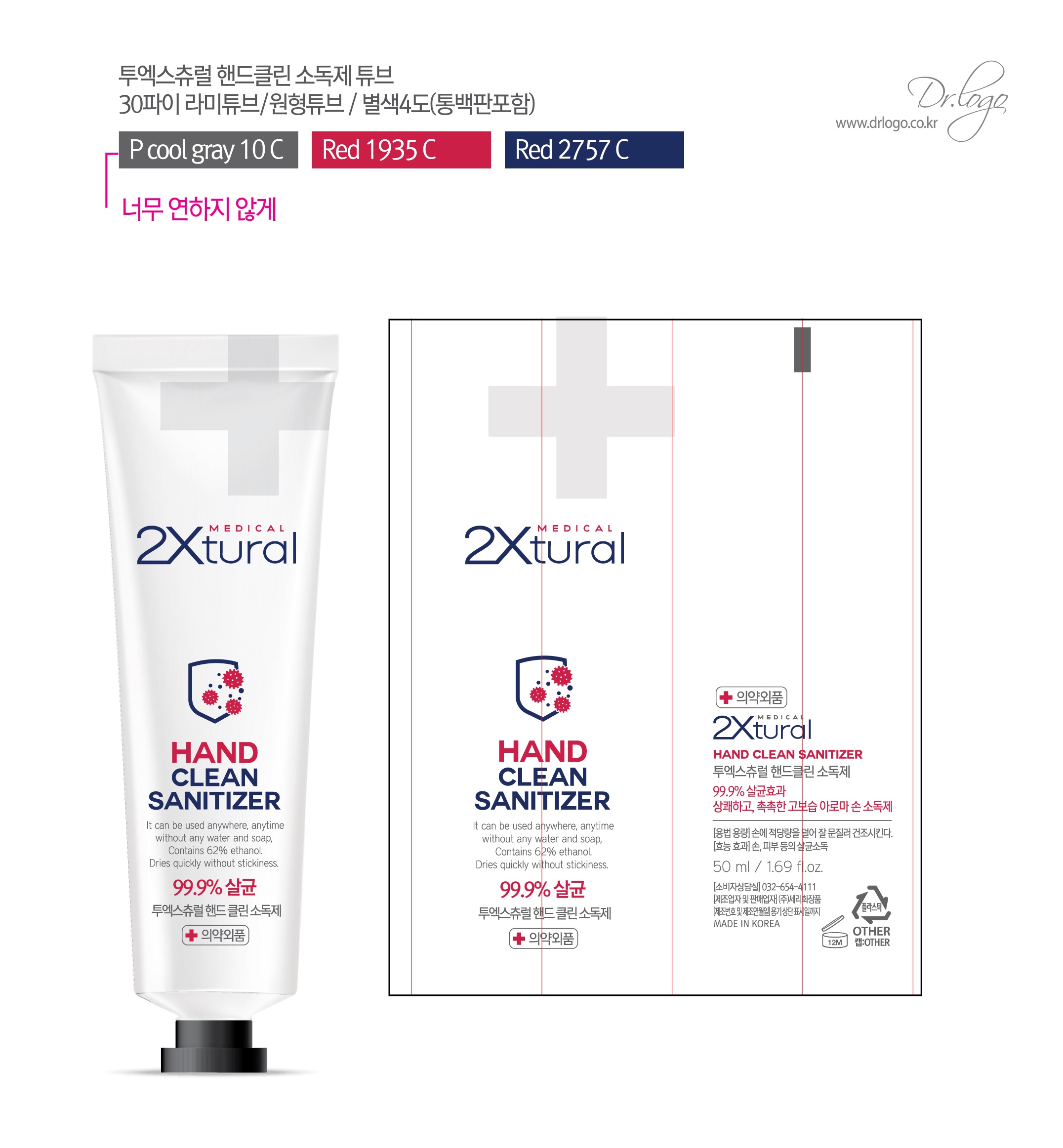 DRUG LABEL: 2XturalPlus Hand Clean Sanitizer gel
NDC: 79235-0002 | Form: GEL
Manufacturer: Seri Cosmetics
Category: otc | Type: HUMAN OTC DRUG LABEL
Date: 20200625

ACTIVE INGREDIENTS: ALCOHOL 70 mL/100 mL
INACTIVE INGREDIENTS: TROMETHAMINE; DEXPANTHENOL; BUTYLENE GLYCOL; LAVENDER OIL; CARBOMER 940; WATER; HYALURONATE SODIUM

Drug Facts

ACTIVE INGREDIENT

alcohol

INACTIVE INGREDIENT

Water
Butylene Glycol
Carbomer
dexpanthenol

lavender oil

sodium hyaluronate

tromethamine

PURPOSE

Sterilization of hands and skin

KEEP OUT OF REACH OF THE CHILDREN

INDICATIONS AND USAGE

Apply appropriate amount to skin or hand, or dry by rubbing well.

WARNINGS

■ For external use only.

■ Do not use in eyes.

■ lf swallowed, get medical help promptly.

■ Stop use, ask doctor lf irritation occurs.

■ Keep out of reach of children.

DOSAGE AND ADMINISTRATION

for external use only